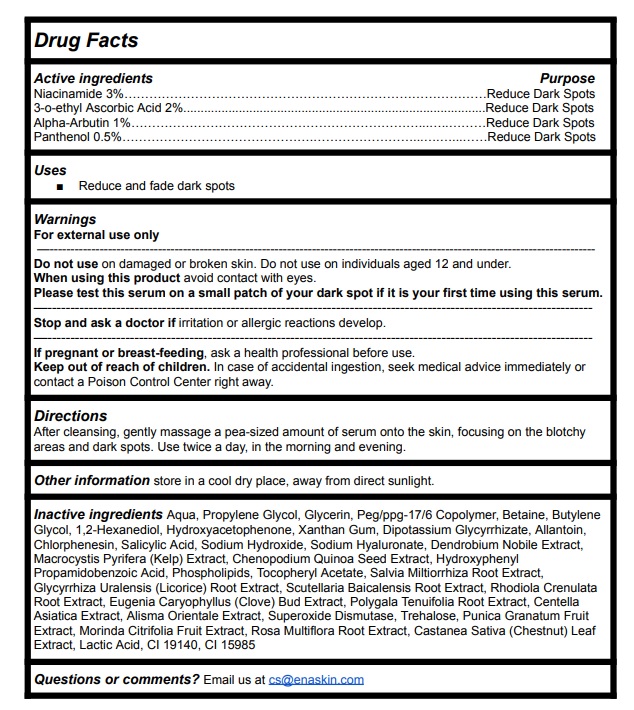 DRUG LABEL: EnaSkin Dark Spot Corrector
NDC: 82898-001 | Form: LIQUID
Manufacturer: EnaSkin LLC
Category: otc | Type: HUMAN OTC DRUG LABEL
Date: 20230411

ACTIVE INGREDIENTS: NIACINAMIDE 3 g/100 mL; 3-O-ETHYL ASCORBIC ACID 2 g/100 mL; ALPHA-ARBUTIN 1 g/100 mL; PANTHENOL 0.5 g/100 mL
INACTIVE INGREDIENTS: WATER; PROPYLENE GLYCOL; GLYCERIN; PEG/PPG-17/6 COPOLYMER; BETAINE; BUTYLENE GLYCOL; 1,2-HEXANEDIOL; HYDROXYACETOPHENONE; XANTHAN GUM; GLYCYRRHIZINATE DIPOTASSIUM; ALLANTOIN; CHLORPHENESIN; SALICYLIC ACID; SODIUM HYDROXIDE; HYALURONATE SODIUM; DENDROBIUM NOBILE WHOLE; MACROCYSTIS PYRIFERA; CHENOPODIUM QUINOA SEED; HYDROXYPHENYL PROPAMIDOBENZOIC ACID; .ALPHA.-TOCOPHEROL ACETATE; SALVIA MILTIORRHIZA ROOT; GLYCYRRHIZA URALENSIS ROOT; SCUTELLARIA BAICALENSIS ROOT; RHODIOLA CRENULATA ROOT; CLOVE; POLYGALA TENUIFOLIA ROOT; CENTELLA ASIATICA TRITERPENOIDS; ALISMA PLANTAGO-AQUATICA SUBSP. ORIENTALE WHOLE; SUPEROXIDE DISMUTASE (SACCHAROMYCES CEREVISIAE); TREHALOSE; POMEGRANATE; NONI FRUIT; ROSA MULTIFLORA ROOT; CASTANEA SATIVA LEAF; LACTIC ACID, UNSPECIFIED FORM; FD&C YELLOW NO. 5; FD&C YELLOW NO. 6; PORACTANT ALFA

Active ingredients Purpose

Niacinamide 3%.......................................................................................Reduce Dark Spots
3-o-ethyl Ascorbic Acid 2%.........................................................................Reduce Dark Spots
Alpha-Arbutin 1%......................................................................................Reduce Dark Spots
Panthenol 0.5%.........................................................................................Reduce Dark Spots

Uses

Reduce and fade dark spots

Warnings

For external use only
Do not use on damaged or broken skin. Do not use on individuals aged 12 and under.

When using this product avoid contact with eyes.

Please test this serum on a small patch of your dark spot if it is your first time using this serum.
Stop and ask a doctor if irritation or allergic reactions develop.
If pregnant or breast-feeding, ask a health professional before use.

Keep out of reach of children. In case of accidental ingestion, seek medical advice immediately or
contact a Poison Control Center right away.

Directions

After cleansing, gently massage a pea-sized amount of serum onto the skin, focusing on the blotchy areas and dark spots.

Use twice a day, in the morning and evening.

Other information

store in a cool dry place, away from direct sunlight.

Inactive ingredients

Aqua, Propylene Glycol, Glycerin, Peg/ppg-17/6 Copolymer, Betaine, Butylene Glycol, 1,2-Hexanediol, Hydroxyacetophenone, Xanthan Gum, Dipotassium Glycyrrhizate, Allantoin, Chlorphenesin, Salicylic Acid, Sodium Hydroxide, Sodium Hyaluronate, Dendrobium Nobile Extract,
Macrocystis Pyrifera (Kelp) Extract, Chenopodium Quinoa Seed Extract, Hydroxyphenyl Propamidobenzoic Acid, Phospholipids, Tocopheryl Acetate, Salvia Miltiorrhiza Root Extract, Glycyrrhiza Uralensis (Licorice) Root Extract, Scutellaria Baicalensis Root Extract, Rhodiola Crenulata
Root Extract, Eugenia Caryophyllus (Clove) Bud Extract, Polygala Tenuifolia Root Extract, Centella Asiatica Extract, Alisma Orientale Extract, Superoxide Dismutase, Trehalose, Punica Granatum Fruit Extract, Morinda Citrifolia Fruit Extract, Rosa Multiflora Root Extract, Castanea Sativa (Chestnut) Leaf Extract, Lactic Acid, CI 19140, CI 15985

Questions or comments?

Email us at cs@enaskin.com